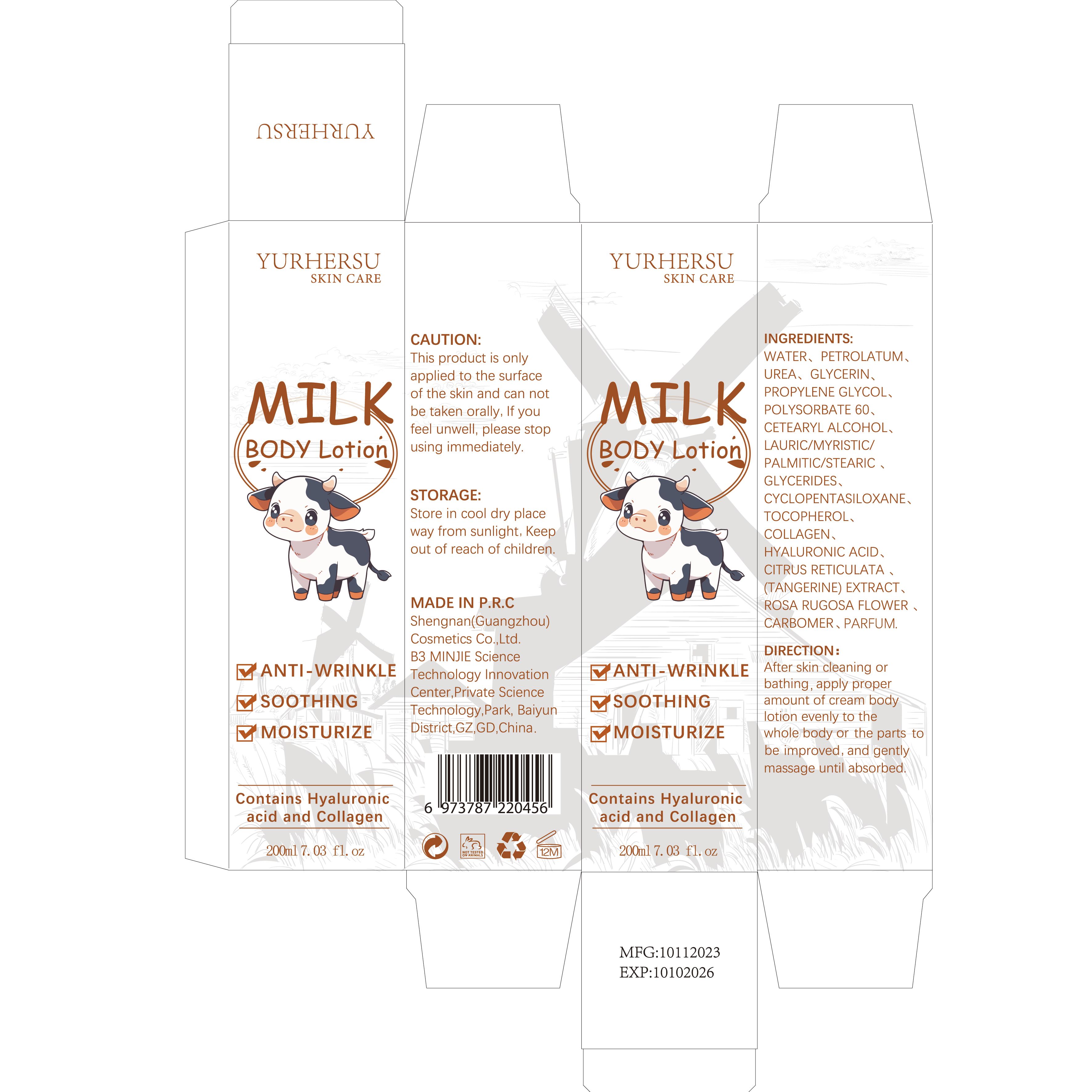 DRUG LABEL: MILKBODyLotion
NDC: 84019-024 | Form: CREAM
Manufacturer: Shengnan (Guangzhou) Cosmetics Co., LTD
Category: otc | Type: HUMAN OTC DRUG LABEL
Date: 20250103

ACTIVE INGREDIENTS: (HYDROXYMETHYL)UREA 100 mg/1 mL
INACTIVE INGREDIENTS: TOCOPHEROL; CYCLOPENTASILOXANE; CETEARYL ALCOHOL; GLYCERIN; PETROLATUM; POLYSORBATE 60; HYALURONIC ACID; CARBOMER; WATER

MILK BODY Lotion

WARNINGS

This product is onlyapplied to the surfaceof the skin and can notbe taken orally.

PURPOSE

Milk body lotion can effectively moisturize the skin, provide necessary hydration, and prevent dryness and flakiness.

STOP USE

Milk body lotion can effectively moisturize the skin, provide necessary hydration, and prevent dryness and flakiness.

ACTIVE INGREDIENT

Urea

WHEN USING

Please clean your hands before use to ensure the best results fromthe product.

INACTIVE INGREDIENT

Water
Glycerin
Petrolatum
Propylene Glycol
Polysorbate 60
Cyclopentasiloxane
Lauric/Myristic/Palmitic/Stearic Glycerides
Cetearyl Alcohol
Fragrance
Tocopherol
Collagen
Hyaluronic Acid
Carbomer
Citrus Reticulata (Tangerine) Extract
Rosa Rugosa Flower Extract

DOSAGE AND ADMINISTRATION

Apply 1 times a day

INDICATIONS AND USAGE

When using body lotion, it is best to apply it evenly and carefully to ensure uniform protection and hydration of the skin, and to maintain the balance water and oil on the skin.